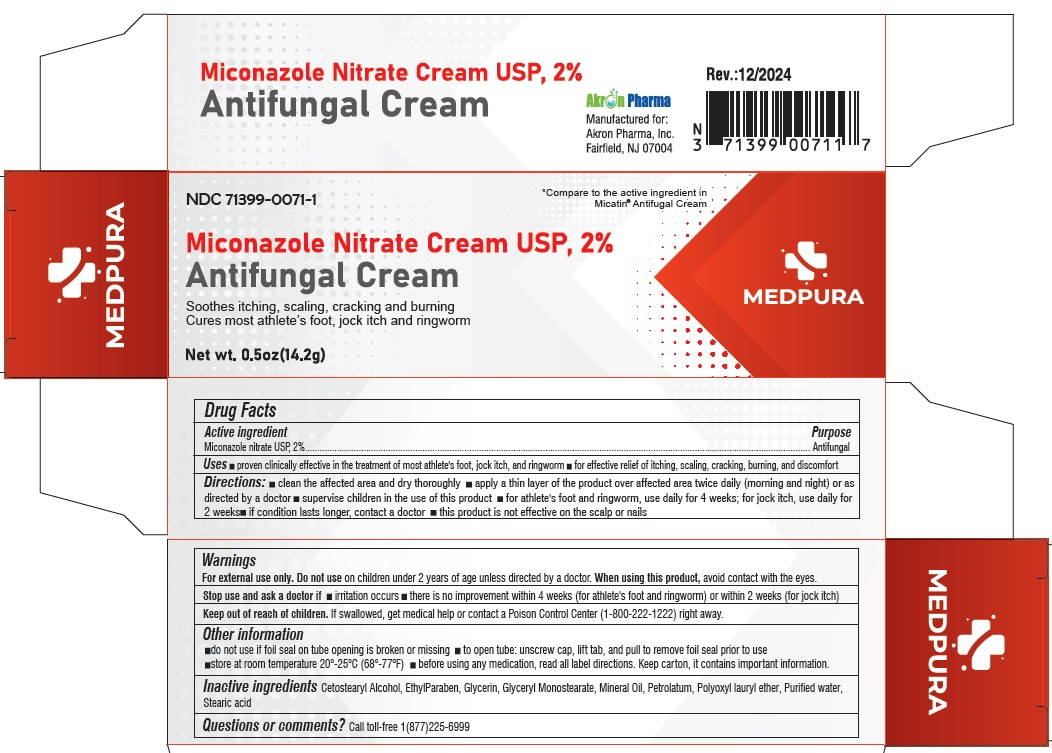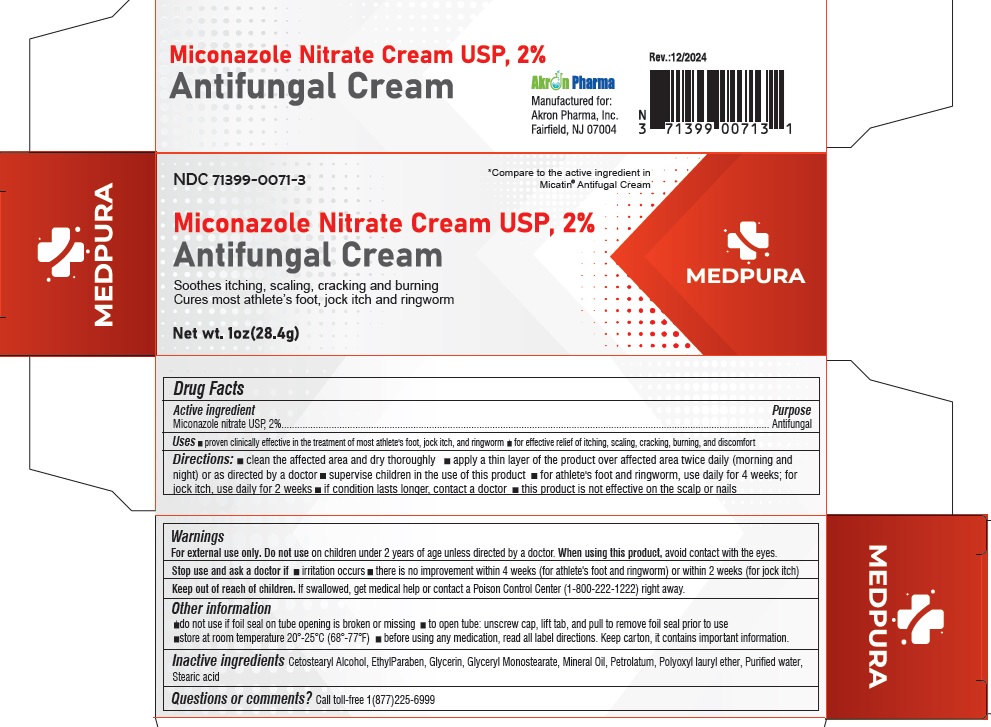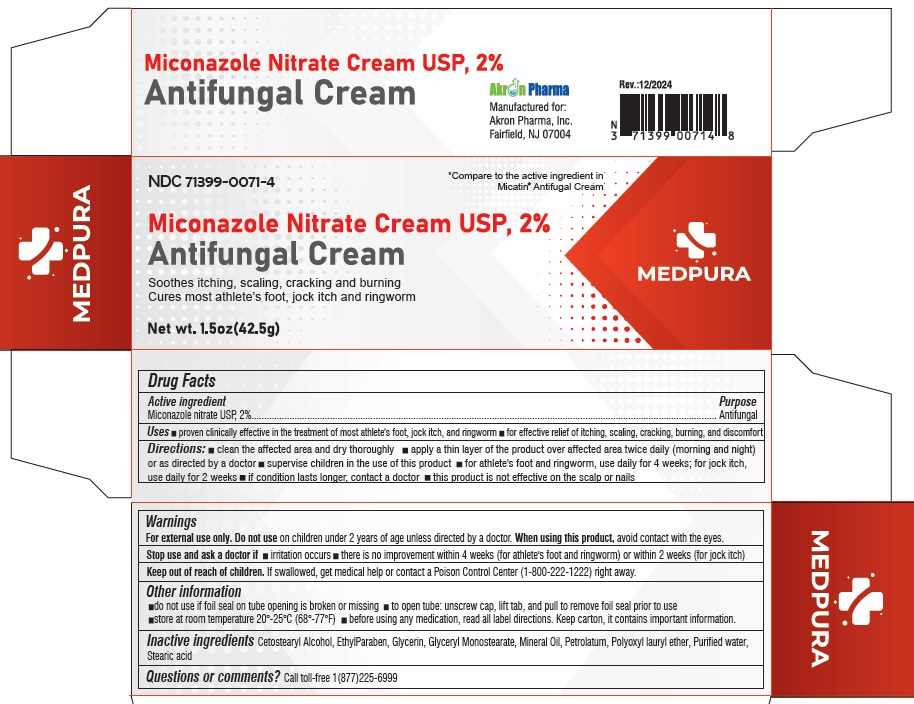 DRUG LABEL: MICONAZOLE Nitrate 2%
NDC: 71399-0071 | Form: CREAM
Manufacturer: Akron Pharma Inc.
Category: otc | Type: HUMAN OTC DRUG LABEL
Date: 20250110

ACTIVE INGREDIENTS: MICONAZOLE NITRATE 2 g/100 g
INACTIVE INGREDIENTS: CETOSTEARYL ALCOHOL; ETHYLPARABEN; GLYCERIN; GLYCERYL MONOSTEARATE; MINERAL OIL; PETROLATUM; LAURETH-23; WATER; STEARIC ACID

MEDPURA MICONAZOLE Nitrate 2%
ANTIFUNGAL CREAM
Soothes itching, scaling, cracking and burning
Cures most athlete’s foot, jock itch and ringworm

Active ingredient

Miconazole Nitrate, USP 2%

Purpose

Anti-Fungal

Uses

- proven clinically effective in the treatment of most athlete's foot, jock itch, and ringworm
- for effective relief of itching, scaling, cracking, burning, and discomfort

Directions

- clean the affected area and dry thoroughly
- apply a thin layer of the product over affected area twice daily (morning and night) or as directed by a doctor + supervise children in the use of this product
- for athlete's foot and ringworm, use daily for 4 weeks; for jock itch, use daily for 2 weeks
- if condition lasts longer, contact a doctor + this product is not effective on the scalp or nails

Warnings

For external use only. Do not use on children under 2 years of age unless directed by a doctor.

When using this product, avoid contact with the eyes.

Stop use and ask a doctor if

- irritation occurs
- there is no improvement within 4 weeks (for athlete's foot and ringworm) or within 2 weeks (for jock itch)

Keep out of reach of children. If swallowed, get medical help or contact a Poison Control Center (1-800-222-1222) right away.

Other Information

- do not use if foil seal on tube opening is broken or missing
- to open tube: unscrew cap, lift tab, and pull to remove foil seal prior to use
- store at room temperature 20°-25°C (68°-77°F)
- before using any medication, read all label directions. Keep carton, it contains important information.

INACTIVE INGREDIENT

Inactive ingredients Cetostearyl Alcohol, EthylParaben, Glycerin, Glyceryl Monostearate, Mineral Oil, Petrolatum, Polyoxyl lauryl ether, Purified water, Stearic acid

QUESTIONS

Call toll-free 1(877)225-6999

Manufactured for:

Akron Pharma, Inc.

Fairfield, NJ 07004